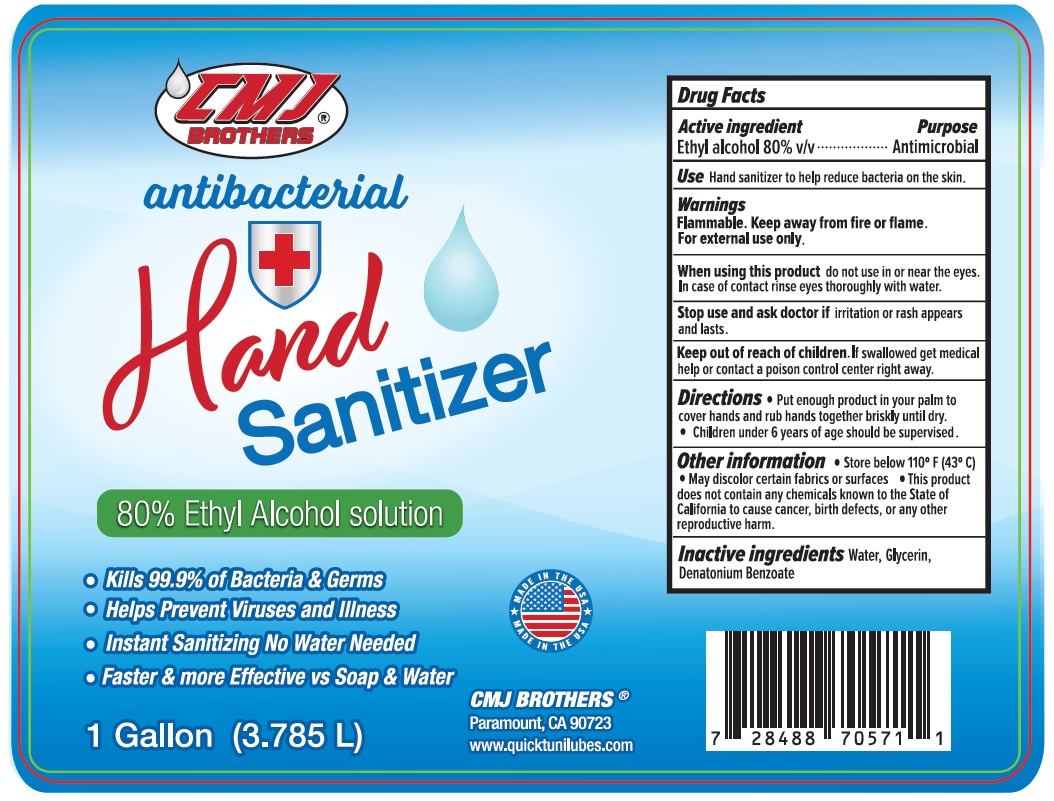 DRUG LABEL: CMJ BROTHERS HAND SANITIZER
NDC: 76722-100 | Form: SOLUTION
Manufacturer: C M J Brother's Corp
Category: otc | Type: HUMAN OTC DRUG LABEL
Date: 20200425

ACTIVE INGREDIENTS: ALCOHOL 80 mL/100 mL
INACTIVE INGREDIENTS: WATER; GLYCERIN; DENATONIUM BENZOATE

CMJ BROTHERS® Hand Sanitizer

Active ingredient

Ethyl alcohol 80% v/v

Purpose

Antimicrobial

Use

Hand sanitizer to help reduce bacteria on the skin.

Warnings

Flammable. Keep away from fire or flame.

For external use only.

When using this product do not use in or near the eyes. In case of contact rinse eyes thoroughly with water.

Stop use and ask a doctor if irritation or rash appears and lasts.

Keep out of reach of children. If swallowed get medical help or contact a poison control center right away.

Directions

- Put enough product in your palm to cover hands and rub hands together briskly until dry.
- Children under 6 years of age should be surprised.

Other information

• Store below 110°F (43°C) • May discolor certain fabrics or surfaces • This product does not contain any chemicals known to the state of California to cause cancer, birth defects, or any other reproductive harm.

Inactive ingredients

Water, Glycerin, Denatonium Benzoate

- Kills 99.9% of Bacteria & Germs
- Helps Prevent Viruses and Illness
- Instant Sanitizing No Water Needed
- Faster & more Effective vs Soap & Water

MADE IN THE USA

CMJ BROTHERS®

Paramount, CA 90723

www.quicktunilubes.com